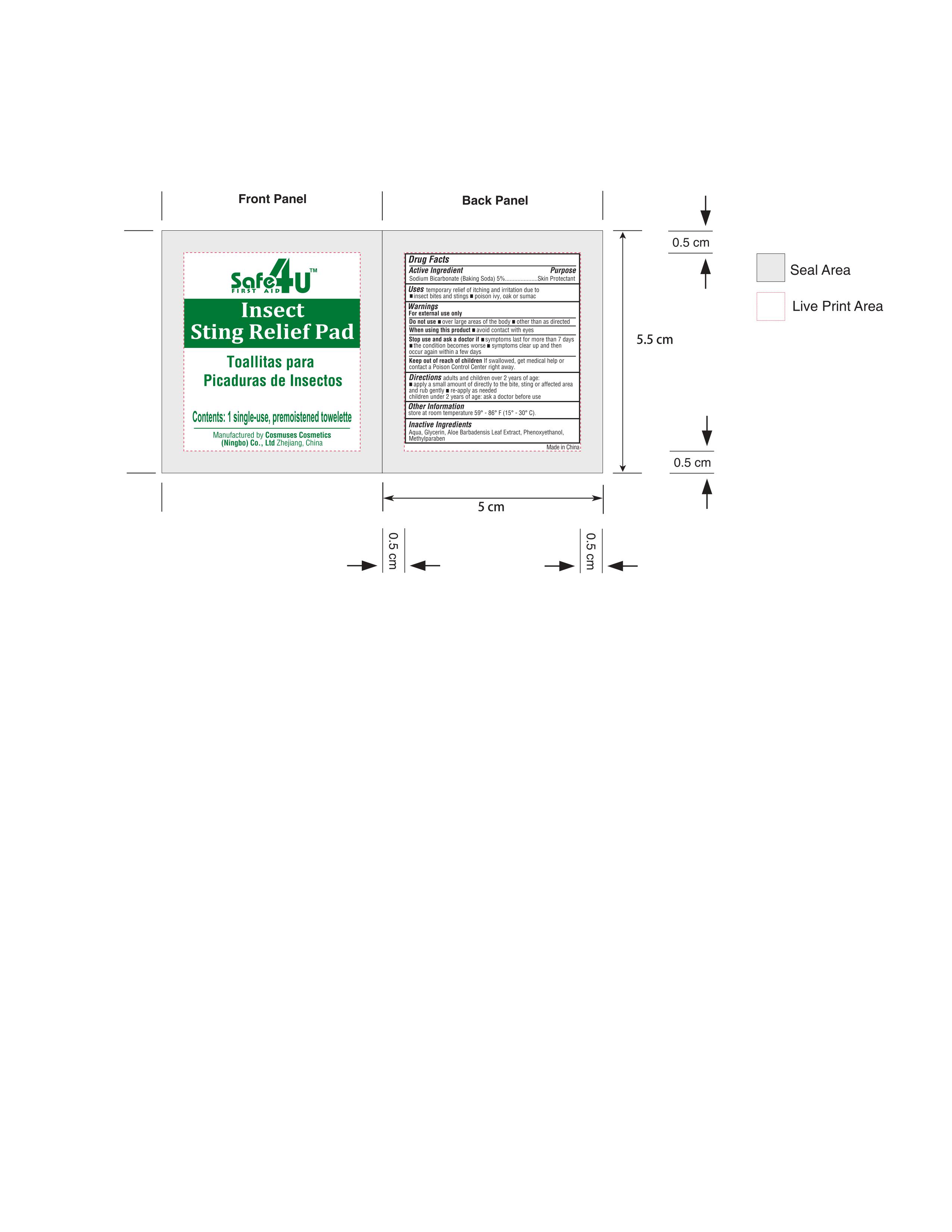 DRUG LABEL: Insect sting relief pad
NDC: 82953-019 | Form: CLOTH
Manufacturer: Cosmuses Cosmetics (Ningbo) Co., Ltd.
Category: otc | Type: HUMAN OTC DRUG LABEL
Date: 20240617

ACTIVE INGREDIENTS: SODIUM BICARBONATE 0.05 g/1 1
INACTIVE INGREDIENTS: GLYCERIN; WATER; ALOE VERA LEAF; PHENOXYETHANOL; METHYLPARABEN

insect sting relief pad

Drug Fact

Active Ingredient

Sodium bicarbonate (Baking Soda) 5%

Purpose

Skin Protectant

Uses

temporary relief of itching and irritation due to

- insect bites and stings
- poison ivy, oak or sumac

Warnings

- For external use only.

Do not use

- over large areas of the body
- other than as directed

When using this product

- avoid contact with eyes

Stop use and ask a doctor if

- symptoms last for more than 7 days
- the condiction becomes worse
- symptoms clear up and then occur again within a few days

Keep out of reach of children if swallowed, get medical help or contact a poison control center right away.

Directions

adults and children over 2 years of age:

- apply a small around of directly to the bite, sting or affected area and rub gently
- re-apply as needed
- children under 2 years of age: ask a doctor before use

other information

store at room temperature: 59℉-86℉ (15℃-30℃)

Inactive Ingredients

Aqua, Glycerin, Aloe Barbadensis Leaf Extract, Phenoxyethanol, Methylparaben.